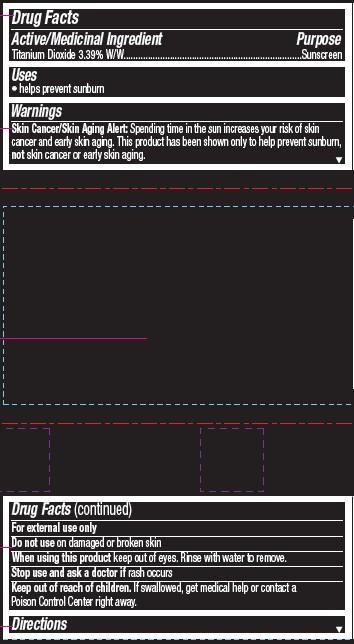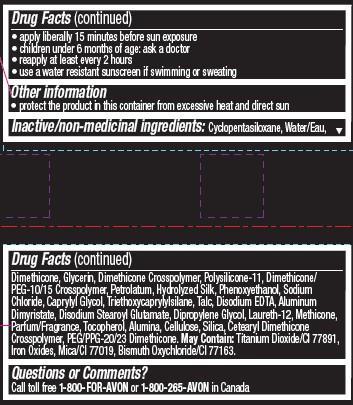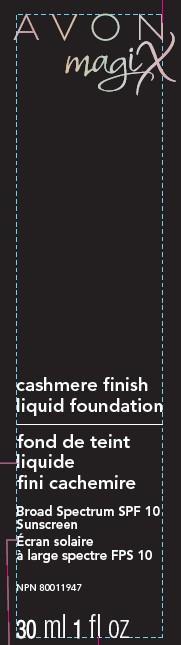 DRUG LABEL: magix
NDC: 10096-0189 | Form: LOTION
Manufacturer: Avon Products, Inc
Category: otc | Type: HUMAN OTC DRUG LABEL
Date: 20091229

ACTIVE INGREDIENTS: TITANIUM DIOXIDE 33.9 mg/1 mL

Active/Medicinal Ingredient
Titanium Dioxide 3.39% W/W...............................

Purpose
.....................................Sunscreen

Uses
• helps prevent sunburn

Warnings
Skin Cancer/Skin Aging Alert: Spending time in the sun increases your risk of skin cancer and early skin aging. This product has been shown only to help prevent sunburn, not skin cancer or early skin aging.

For external use only

Do not use on damaged or broken skin

When using this product keep out of eyes. Rinse with water to remove.

Stop use and ask a doctor if rash occurs

Keep out of reach of children. If swallowed, get medical help or contact a Poison Control Center right away.

Directions

• apply liberally 15 minutes before sun exposure
• children under 6 months of age: ask a doctor
• reapply at least every 2 hours
• use a water resistant sunscreen if swimming or sweating

Other information
• protect the product in this container from excessive heat and direct sun

INACTIVE INGREDIENT

Inactive/non-medicinal ingredients: Cyclopentasiloxane, Water/Eau,Dimethicone, Glycerin, Dimethicone Crosspolymer, Polysilicone-11, Dimethicone/PEG-10/15 Crosspolymer, Petrolatum, Hydrolyzed Silk, Phenoxyethanol, Sodium Chloride, Caprylyl Glycol, Triethoxycaprylylsilane, Talc, Disodium EDTA, Aluminum Dimyristate, Disodium Stearoyl Glutamate, Dipropylene Glycol, Laureth-12, Methicone, Parfum/Fragrance, Tocopherol, Alumina, Cellulose, Silica, Cetearyl Dimethicone Crosspolymer, PEG/PPG-20/23 Dimethicone. May Contain: Titanium Dioxide/CI 77891, Iron Oxides, Mica/CI 77019, Bismuth Oxychloride/CI 77163.

Questions or Comments?
Call toll free 1-800-FOR-AVON or 1-800-265-AVON in Canada